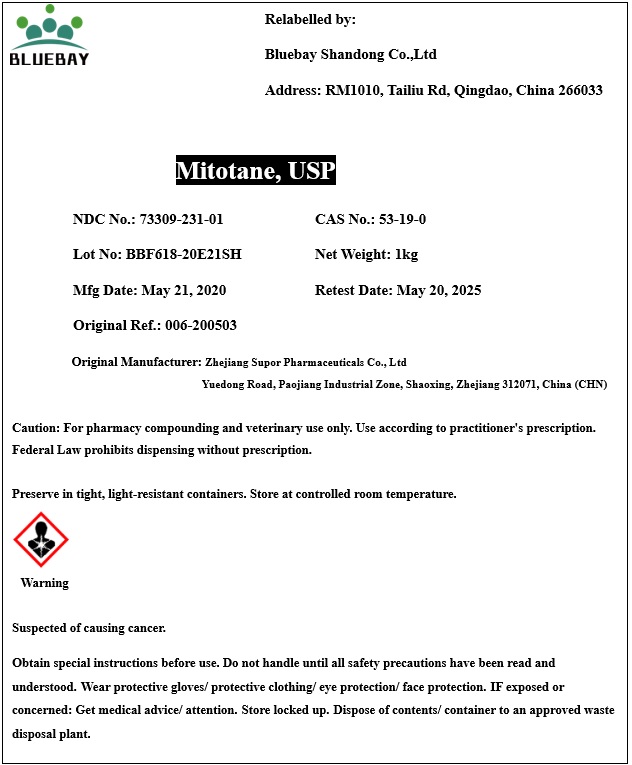 DRUG LABEL: Mitotane
NDC: 73309-231 | Form: POWDER
Manufacturer: BLUEBAY SHANDONG CO.,LTD
Category: other | Type: BULK INGREDIENT
Date: 20201230

ACTIVE INGREDIENTS: MITOTANE 1 kg/1 kg

Mitotane